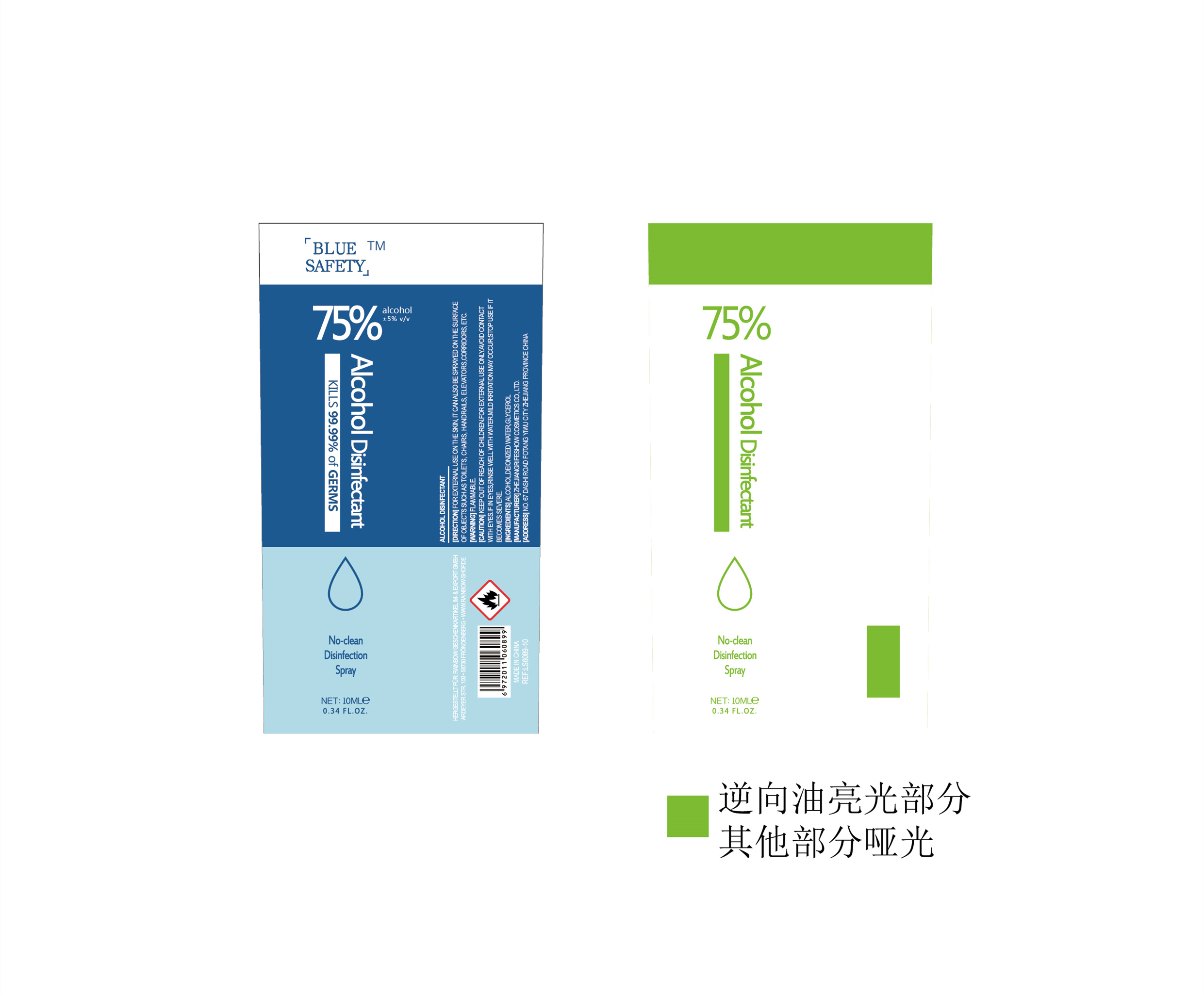 DRUG LABEL: 75%Alcohol disinfectant
NDC: 56084-013 | Form: GEL
Manufacturer: ZHEJIANG RIFESHOW COSMETICS CO.,LTD
Category: otc | Type: HUMAN OTC DRUG LABEL
Date: 20200512

ACTIVE INGREDIENTS: ALCOHOL 6.8 mL/10 mL
INACTIVE INGREDIENTS: TROLAMINE; GLYCERIN; WATER; 5-NORBORNENE-2-METHYLOLACRYLATE

PURPOSE

Effective disinfection reached 99.9%

ACTIVE INGREDIENT

Alcohol

INDICATIONS AND USAGE

SUITABLE FOR HAND SURFACE CLEANING DISINFECTION

keep out of children

WARNINGS

1.THS PRODUCT 5 FOR EXTERNAL USE OF DISPOSABLE HAND DISINFECTION CONDENSATION, NOT FOR INTERNAL USE KEEP OUTOF REACHOF CHILDREN.
2. THS PRODUCT SLGHTLY RRTATES THE DAMAGEDSKON.
3.STORE IN SEALED, COOL, DRY PLACE.AVOID THE SUN AND INFLAMMBLE DURING TRANSPORTATION.

DOSAGE AND ADMINISTRATION

LSAGE TAKE APPROPRIATE AMOUNT OF THIS PRODUCT ON THEPAIMAND THEN KNEADWPEPALMS,BACXOFHANDS, FNGERS. BACK OF RNGERS, THUMB.FINGERIPSANDWRISTS, UNIL HANDS AREDRY.

INACTIVE INGREDIENT

Deionized water
Glycerol
Carbopol 940
Triethanolamine